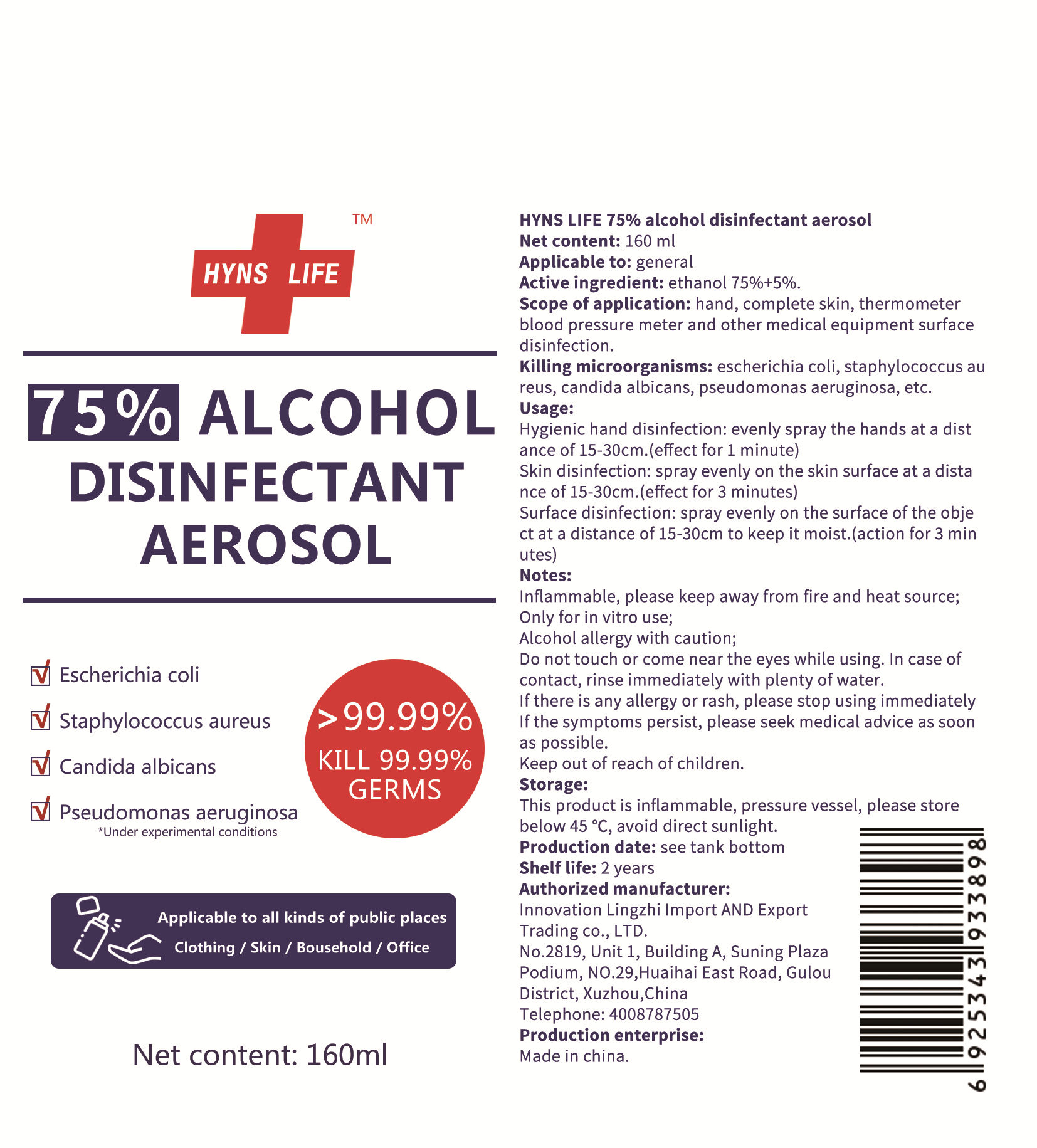 DRUG LABEL: alcohol disinfectant
NDC: 55454-001 | Form: AEROSOL
Manufacturer: INNOVATION LINGZHI IMPORT AND EXPORT TRADING CO.，LTD.
Category: otc | Type: HUMAN OTC DRUG LABEL
Date: 20200403

ACTIVE INGREDIENTS: ALCOHOL 120 mL/160 mL
INACTIVE INGREDIENTS: WATER

ACTIVE INGREDIENT

ethanol 75%+5%

DOSAGE AND ADMINISTRATION

This product is inflammable, pressure vessel, please store below 45°C, avoid direct sunlight.

WARNINGS

Inflammable, please keep away from fire and heat source;
Only for in vitro use;
Alcohol allergy with caution;
Do not touch or come near the eyes while using. In case of contact, rinse immediately with plenty of water.
If there is any allergy or rash, please stop using immediately
If the symptoms persist, please seek medical advice as soon as possible.

PURPOSE

Disinfection

Sterilization

No Rinseing

keep out of reach of children section

INDICATIONS AND USAGE

Hygienic hand disinfection: evenly spray the hands at a distance of 15-30cm.(effect for 1 minute).

Skin disinfection: spray evenly on the skin surface at a distance of 15-30cm.(effect for 3 minutes)

Surface disinfection: spray evenly on the surface of the object at a distance of 15-30cm to keep it moist.(action for 3 minutes).

INACTIVE INGREDIENT

water